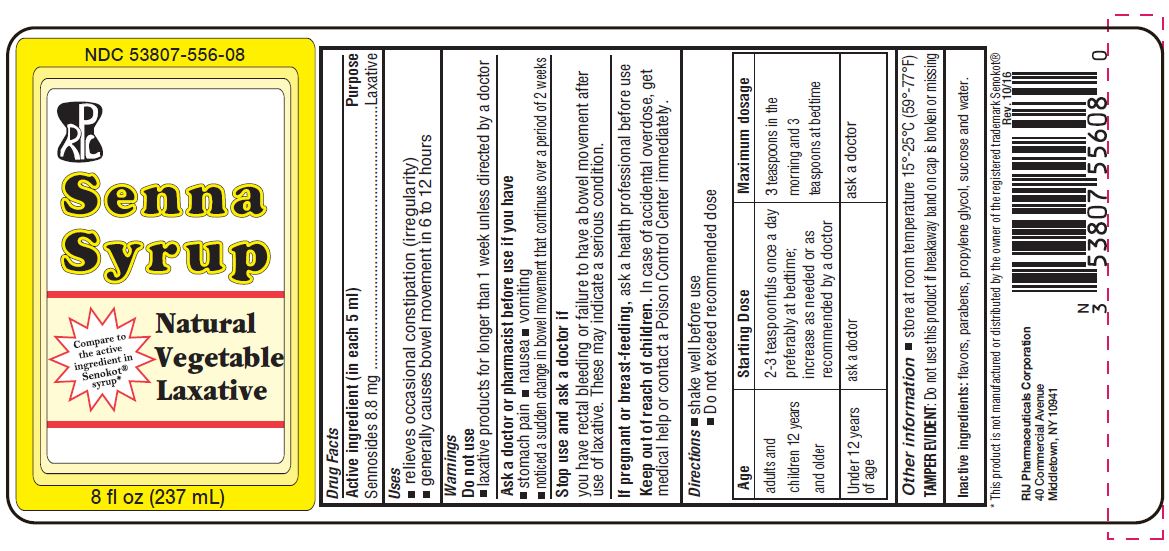 DRUG LABEL: Senna
NDC: 53807-556 | Form: SYRUP
Manufacturer: Rij Pharmaceutical Corporation
Category: otc | Type: HUMAN OTC DRUG LABEL
Date: 20180430

ACTIVE INGREDIENTS: Sennosides A and B 8.8 mg/5 mL
INACTIVE INGREDIENTS: Methylparaben; propylene glycol; propylparaben; water; cocoa; sucrose

Senna Syrup

Drug Facts

Active Ingredient (in each teaspoonful)

Sennosides 8.8 mg

Purpose

Laxative

Uses

- relieves occasional constipation (irregularity)
- generally produces bowel movement in 6-12 hours

Warnings

Do not use

- laxative products for longer than 1 week unless directed by a doctor

Ask a doctor before use if you have

- stomach pain
- nausea
- vomiting
- noticed a sudden change in bowel movements that continues over a period of 2 weeks

Stop use and ask a doctor if you have rectal bleeding or fail to have bowel movement after use of laxative. These may indicate a serious condition.

PREGNANCY OR BREAST FEEDING

If pregnant or breast-feeding, ask a professional before use.

Keep out of reach of children. In case of accidental overdose, get medical help or contact a Poison Control Center right away.

Directions

- shake well before use
- Do not exceed recommended dose

Age | Starting Dose | Maximum dosage
adults and children 12 years and older | 2 - 3 teaspoons once a day preferable at bedtime; increase as needed or as recommended by a doctor | 3 teaspoons in the morning and 3 teaspoons at bedtime
Under 12 years of age | ask a doctor | ask a doctor

Other information

- store at room temperature 15°- 25°C (59°- 77°F)

TAMPER EVIDENT: Do not use this product if breakaway band on cap is broken or missing.

Inactive ingredients

flavors, parabens, propylene glycol, sucrose, and water.

RIJ Pharmaceuticals Corporation
40 Commercial Avenue
Middletown, NY 10941

PRINCIPAL DISPLAY PANEL - 237 mL Bottle Label

NDC 53807-556-08

Senna Syrup
Senna Syrup
Natural Vegetable Laxative

8 fl. oz. (237 mL)